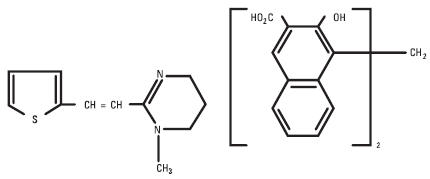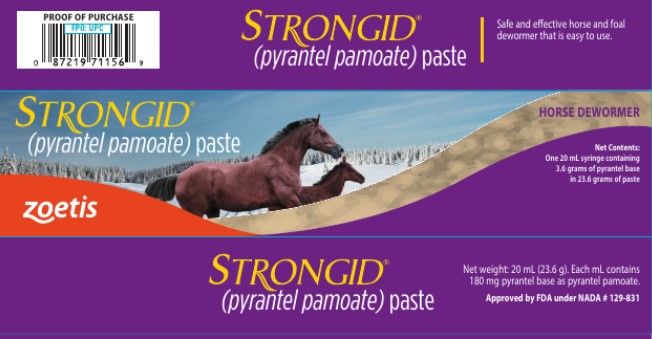 DRUG LABEL: Strongid
NDC: 54771-2410 | Form: PASTE
Manufacturer: Zoetis Inc.
Category: animal | Type: OTC ANIMAL DRUG LABEL
Date: 20260127

ACTIVE INGREDIENTS: PYRANTEL PAMOATE 180 mg/1 mL

Strongid®
(pyrantel pamoate) paste

Horse Dewormer

Read Entire Package Insert Carefully Before Using This Product

DESCRIPTION

Strongid Paste is a pale yellow to buff paste containing 43.9% w/w pyrantel pamoate in an inert vehicle. Each syringe contains 3.6 grams of pyrantel base in 23.6 grams (20 mL) paste. Each mL contains 180 mg pyrantel base as pyrantel pamoate.

Composition

Pyrantel pamoate is a compound belonging to a family classified chemically as tetrahydropyrimidines. It is a yellow, water-insoluble crystalline salt of the tetrahydropyrimidine base and pamoic acid containing 34.7% base activity. The chemical structure and name are given below.

Chemical name: (E)-1,4,5,6-tetrahydro-1-methyl-2-[2-(2-thienyl)-vinyl]-pyrimidine 4,4' methylenebis [3-hydroxy-2-naphtholate] (1:1)

INDICATIONS FOR USE

For the removal and control of mature infections of large strongyles (Strongylus vulgaris, S. edentatus, S. equinus); small strongyles; pinworms (Oxyuris equi); and large roundworms (Parascaris equorum) in horses and ponies.

Consult your veterinarian for assistance in the diagnosis, treatment, and control of parasitism.

DOSAGE AND TREATMENT

Strongid Paste is to be administered as a single oral dose of 3 mg pyrantel base per lb of body weight. The syringe has 4 weight mark increments. Each weight mark indicates the recommended dose for 300 lb of body weight.

 | Dosage
Body Weight Range | Volume | mg Pyrantel Base
up to 300 lb | 1/4 syringe (5 mL) | 900 mg
301-600 lb | 1/2 syringe (10mL) | 1800 mg
601-900 lb | 3/4 syringe (15 mL) | 2700 mg
901-1200 lb | 1 full syringe (20 mL) | 3600 mg

Note: Position screw-gauge over appropriate mark on plunger. Each mL contains 180 mg of pyrantel base as pyrantel pamoate.

Do not underdose. Ensure each animal receives a complete dose based on a current body weight. Underdosing may result in ineffective treatment, and encourage the development of parasite resistance.

For maximum control of parasitism, it is recommended that foals (2–8 months of age) be dosed every 4 weeks. To minimize the potential source of infection that the mare may pose to the foal, the mare should be treated 1 month prior to anticipated foaling date followed by retreatment 10 days to 2 weeks after birth of foal. Horses and ponies over 8 months of age should be routinely dosed every 6 weeks.

ADMINISTRATION

After removing the cap, the paste should be deposited on the dorsum of the tongue. Introduce the nozzle end of the syringe at the corner of the mouth. Direct the syringe backwards and depress the plunger to deposit the paste onto the tongue. Given in this manner, it is unlikely that rejection of the paste will occur. Raising the horse's head sometimes assists in the swallowing process. When only part of the paste has been used, replace the cap on the syringe nozzle.

EFFICACY

Critical (worm count) studies in horses demonstrated that Strongid Paste administered at the recommended dosage was efficacious against mature infections of Strongylus vulgaris (>90%), S. edentatus (69%), S. equinus (>90%), Oxyuris equi (81%), Parascaris equorum (>90%), and small strongyles (>90%).

WARNINGS

Do not use in horses intended for human consumption. Keep out of reach of children.

It is recommended that severely debilitated animals not be treated with this preparation.

OTHER WARNINGS

Parasite resistance may develop to any dewormer, and has been reported for most classes of dewormers. Treatment with a dewormer used in conjunction with parasite management practices appropriate to the geographic area and the animal(s) to be treated may slow the development of parasite resistance. Fecal examinations or other diagnostic tests and parasite management history should be used to determine if the product is appropriate for the herd prior to the use of any dewormer. Following the use of any dewormer, effectiveness of treatment should be monitored (for example, with the use of a fecal egg count reduction test or another appropriate method). A decrease in a drug’s effectiveness over time as calculated by fecal egg count reduction tests may indicate the development of resistance to the dewormer administered. Your parasite management plan should be adjusted accordingly based on regular monitoring.

RECOMMENDED STORAGE

Store at controlled room temperature 15°–25°C (59°–77°F).

Approved by FDA under NADA # 129-831
zoetis
Distributed by:
Zoetis Inc.
Kalamazoo, MI 490
52477600
Revised: November 2025

PRINCIPAL DISPLAY PANEL - 20 mL Syringe Carton

52477800